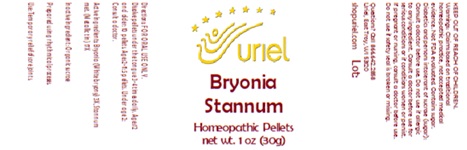 DRUG LABEL: Bryonia Stannum
NDC: 48951-2087 | Form: PELLET
Manufacturer: Uriel Pharmacy Inc.
Category: homeopathic | Type: HUMAN OTC DRUG LABEL
Date: 20260225

ACTIVE INGREDIENTS: BRYONIA ALBA ROOT 3 [hp_X]/1 1; TIN 17 [hp_X]/1 1
INACTIVE INGREDIENTS: SUCROSE

Bryonia Stannum

INDICATIONS AND USAGE

Directions: FOR ORAL USE ONLY.

DOSAGE AND ADMINISTRATION

Dissolve pellets under the tongue 3-4 times daily. Ages 12 and older: 10 pellets. Ages 2-11: 5 pellets. Under age 2: Consult a doctor.

ACTIVE INGREDIENT

Active Ingredients: Bryonia (White bryony) 3X, Stannum met. (Metallic tin) 17X

Inactive Ingredient: Organic sucrose

Prepared using rhythmical processes.

PURPOSE

Use: Temporary relief of sore joints.

KEEP OUT OF REACH OF CHILDREN.

WARNINGS

Warnings: Claims based on traditional homeopathic practice, not accepted medical evidence. Not FDA evaluated. Contains sugar. Diabetics and persons intolerant of sucrose (sugar): Consult a doctor before use. Do not use if allergic to any ingredient. Consult a doctor before use for serious conditions or if conditions worsen or persist. If pregnant or nursing, consult a doctor before use. Do not use if safety seal is broken or missing.

QUESTIONS

Questions? Call 866.642.2858 Uriel, East Troy WI 53120 shopuriel.com

Lot: